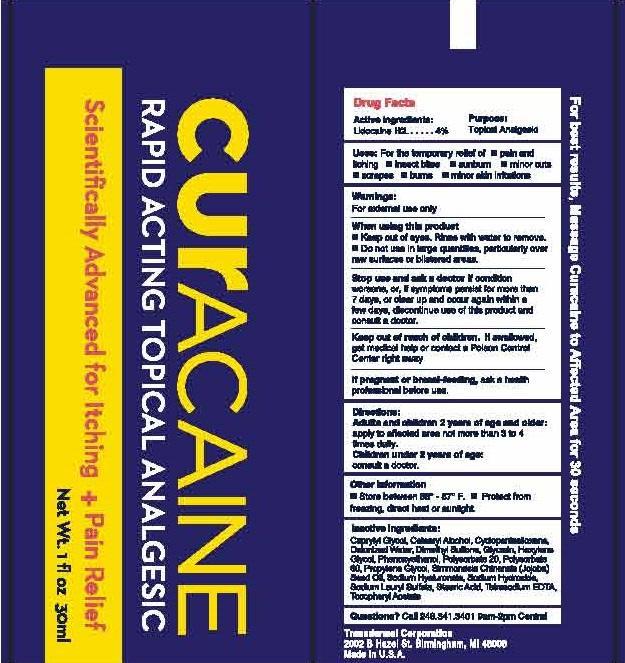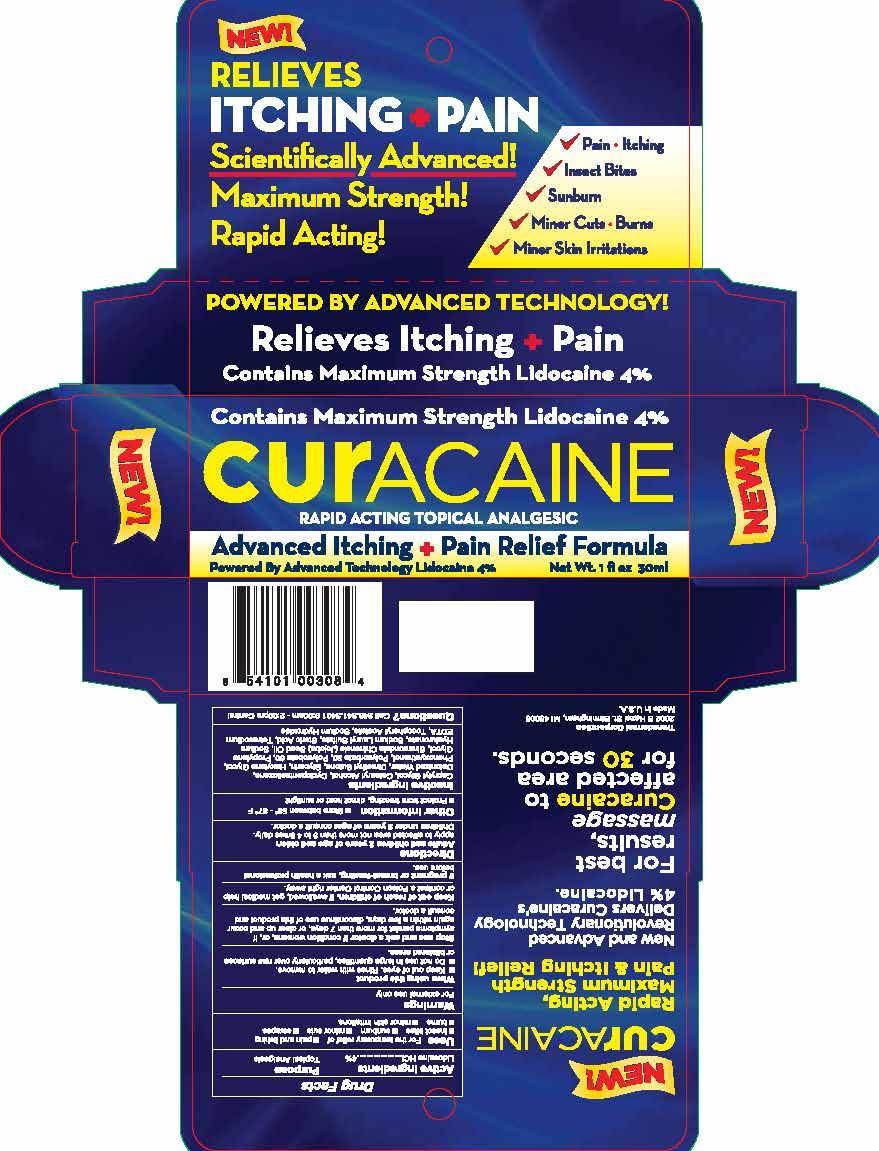 DRUG LABEL: CURACAINE
NDC: 51350-012 | Form: CREAM
Manufacturer: Transdermal Corp
Category: otc | Type: HUMAN OTC DRUG LABEL
Date: 20170214

ACTIVE INGREDIENTS: LIDOCAINE HYDROCHLORIDE 4 g/100 mL
INACTIVE INGREDIENTS: CAPRYLYL GLYCOL; CETOSTEARYL ALCOHOL; CYCLOMETHICONE 5; GLYCERIN; HEXYLENE GLYCOL; PHENOXYETHANOL; POLYSORBATE 20; POLYSORBATE 60; PROPYLENE GLYCOL; JOJOBA OIL; HYALURONATE SODIUM; SODIUM LAURYL SULFATE; EDETATE SODIUM; .ALPHA.-TOCOPHEROL ACETATE; TROLAMINE

Active Ingredients

LIDOCAINE HCL 4%

PURPOSE:

topical analgesic

Keep out of reach of children. If swallowed, get medical help or contact a Poison Control Center right away.

INDICATIONS AND USAGE

Uses for the temporary relief of

- pain and itching
- insect bites
- sunburn
- minor cuts
- scrapes
- burns
- minor skin irritations

Warnings

For external use only

When using this product

- Keep out of eyes. Rinse with water to remove.
- Do not use in large quantities, particularly over raw surfaces or blistered areas.
- If pregnant or breast feeding, ask a health professional before use.

Directions

Adults and children 2 years of age and older:

Apply to affected area not more than 3 to 4 times daily.

Children under 2 years of age: consult a doctor.

Inactive Ingredients

Caprylyl Glycol, Cetearyl Alcohol, Clyclopentasiloxane, Deionized water, Dimethyl Sulone, Glycerin, Hexylene Glycol, Phenoxyethanol, Polysorbate 20, Polysorbate 60, Propylene Glycol, Simmondsia Chinensis (Jojoba) Seed Oil, Sodium hyaluronate, Sodium Lauryl Sulfate Sulfate, Steric Acid, Tetrasodium EDTA, Tocopheryl Acetate, Sodium Hydroxide.

Stop use and ask a doctor if conditions worsens, or, if symptoms persist for more than 7 days, or clear up and occur again within a few days, discontinue use of the product and consult a doctor.

PURPOSE

TOPICAL ANALGESIC

USES:

FOR THE TEMPORARY RELIEF OF

- PAIN AND ITCHING
- INSECT BITES
- SUNBURN
- MINOR CUTS
- SCRAPES
- BURNS
- MINOR SKIN IRRITATIONS

WARNINGS:

FOR EXTERNAL USE ONLY

WHEN USING THIS PRODUCT

- KEEP OUT OF EYES. RINSE WITH WATER TO REMOVE.
- DO NOT USE IN LARGE UANTITIES, PARTICULARLY OVER RAW SURFACES OR BLISTERED AREAS.

STOP USE AND ASK A DOCTOR IF CONDITION WORSENS, OR, IF SYMPTOMS PERSIST FOR MORE THAN 7 DAYS, OR CLEAR UP AND OCCUR AGAIN WITHIN A FEW DAYS, DISCONTINUE USE OF THIS PRODUCT AND CONSULT A DOCTOR.

KEEP OUT OF REACH OF CHILDREN. IF SWALLOWED, GET MEDICAL HELP OR CONTACT A PISON CONTROL CENTER RIGHT AWAY.

PREGNANCY OR BREAST FEEDING

IF PREGNANT OR BREAST FEEDING, ASK A HEALTH PROFESSIONAL BEFORE USE.

DIRECTIONS:

ADULTS AND CHILDREN 2 YEARS OF AGE AND OLDER:

APPLY TO AFFECTED AREA NOT MORE THAN 3 TO 4 TIMES DAILY.

CHILDREN UNDER 2 YEARS OF AGE:

CONSULT A DOCTOR.

OTHER INFORMATION

- STORE BETWEEN 58° - 87° F.
- PROTECT FROM FREEZING, DIRECT HEAT OR SUNLIGHT.

QUESTIONS?

CALL 248.341.3401 9AM-2PM CENTRAL

INACTIVE INGREDIENTS:

CAPRYLYL GLYCOL, CETEARYL ALCOHOL, CYCLOPENTASILOXANE, DEIONIZED WATER, DIMETHYL SULFONE, GLYCERIN, HEXYLENE GLYCOL, PHENOXYETHANOL, POLYSORBATE 20, POLYSORBATE 60, PROPYLENE GLYCOL, SIMMONDSIA CHINENSIS (JOJOBA) SEED OIL, SODIUM HYALURONATE, SODIUM HYDROXIDE, SODIUM LAURYL SULFATE, STEARIC ACID, TETRASODIUM EDTA, TOCOPHERYL ACETATE.